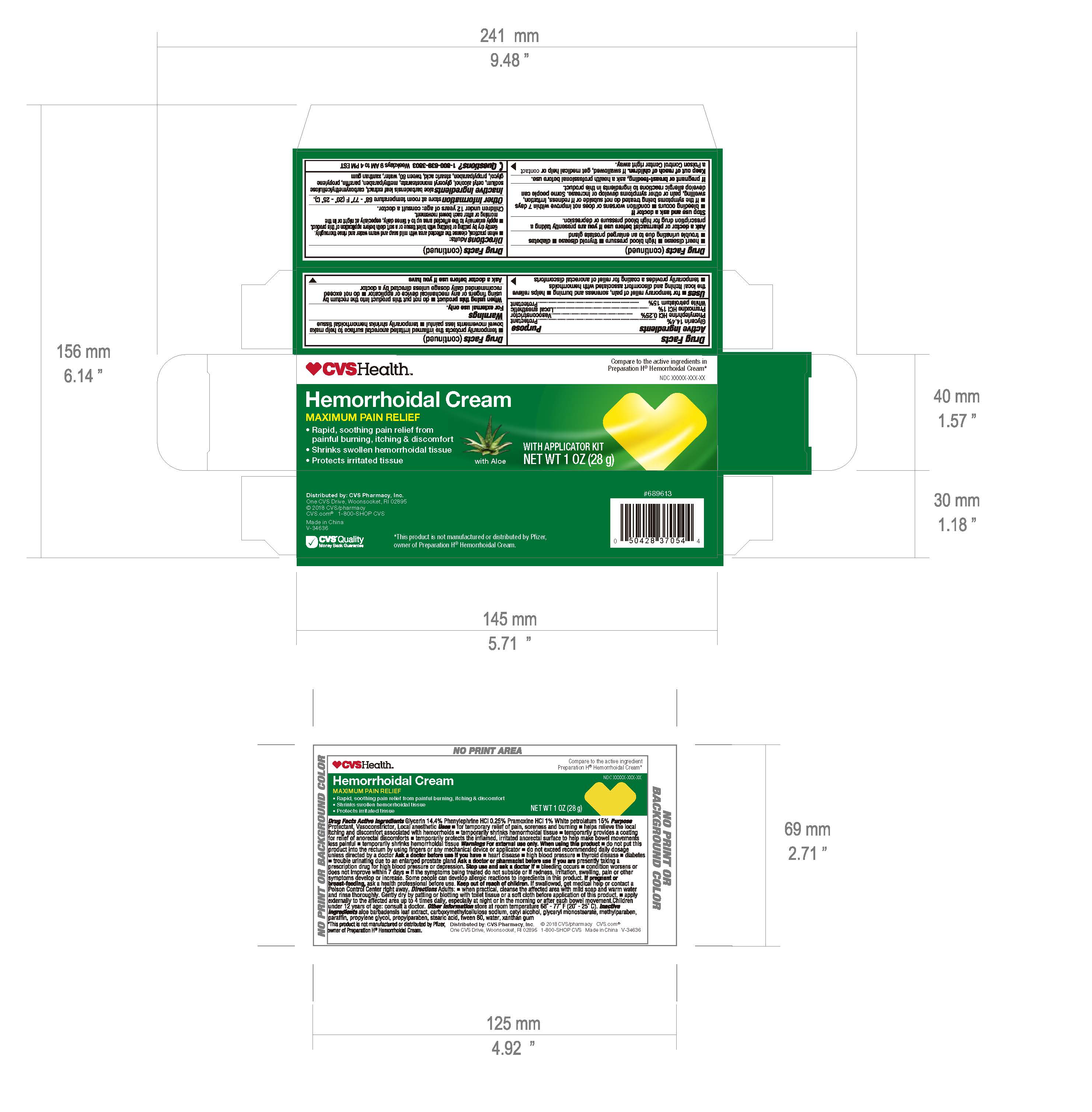 DRUG LABEL: 
                  CVS Health

                
                  

NDC: 69571-010 | Form: CREAM
Manufacturer: FRONT PHARMACEUTICAL PLC
Category: otc | Type: HUMAN OTC DRUG LABEL
Date: 20231026

ACTIVE INGREDIENTS: GLYCERIN 14.4 g/100 g; PHENYLEPHRINE HYDROCHLORIDE 0.25 g/100 g; PRAMOXINE HYDROCHLORIDE 1 g/100 g; PETROLATUM 15 g/100 g
INACTIVE INGREDIENTS: ALOE VERA LEAF; CARBOXYMETHYLCELLULOSE SODIUM; CETYL ALCOHOL; GLYCERYL MONOSTEARATE; METHYLPARABEN; PARAFFIN; PROPYLENE GLYCOL; PROPYLPARABEN; STEARIC ACID; POLYSORBATE 80; WATER; XANTHAN GUM

CVS Health Hemorrhoidal Cream, 28g

Active ingredients

Glycerin 14.4%

Phenylephrine HCl 0.25%

Pramoxine HCl 1%

White petrolatum 15%

Purpose

Glycerin 14.4% ...........................Protectant

Phenylephrine HCl 0.25% .............Vasoconstrictor

Pramoxine HCl 1%........................Local anesthetic

White petrolatum 15%..................Protectant

INDICATIONS AND USAGE

•for temporary relief of pain, soreness and burning •helps relieve Uses

the local itching and discomfort associated ith hemorrhoids

•temporarily provides a coating for f of anorectal discomforts

•temporarily protects the inflamed irritated anorectal surface to help make

bowel movements less painful •temporarily shrinks hemorrhoidal tissue

Warnings

. For external use only

•do not put this product into the rectum by When using this product

using fingers or any mechanical device or applicator •do not exceed

recommended daily dosage unless directed by a doctor

Ask a doctor before use ifyou have

•heart disease •high blood pressure •thyroid disease •diabetes

•trouble urinating due to an enlarged prostate gland

presently taking a Ask a doctor or pharmacist before use if you are

prescription drug for high blood pressure or depsression

Stop use and ask a doctor if

•bleeding occurs •condition worsens or does not improve within 7 days

•if the symptoms being treated do not subside or if redness, irritation,

swelling, pain or other symptoms develop or increase. Some people can

develop allergic reactions to ingredients in this product.

, ask a health professional before use. If pregnant or breast-feeding

KEEP OUT OF REACH OF CHILDREN

. If swallowed, get medical help or contact Keep out of reach of children

a Poison Control Center right away.

DOSAGE AND ADMINISTRATION

Adults: Directions

•when practical, cleanse the affected area with mild soap and water and rinse thoroughly.

Gently dry by patting or blotting with toilet tissue or a soft cloth before application of this product.

•apply externally to the affected area up to 4 times daily, especially at night or in the

morning or after each bowel movement.

Children under 12 years of age: consult a doctor.

STORAGE AND HANDLING

store at room temperature 68° - 77° F (20° - 25° C) Other information

INACTIVE INGREDIENT

aloe barbadensis leaf extract, carboxymethyllcellulose Inactive ingredients

sodium, cetyl alcohol, glyceryl monostearate, methylparaben, paraffin, propylene

glycol, propylparaben, stearic acid, tween 80, water, xanthan gum

QUESTIONS

1-800-639-3803 Weekdays 9 AM to 4 PM EST Questions?